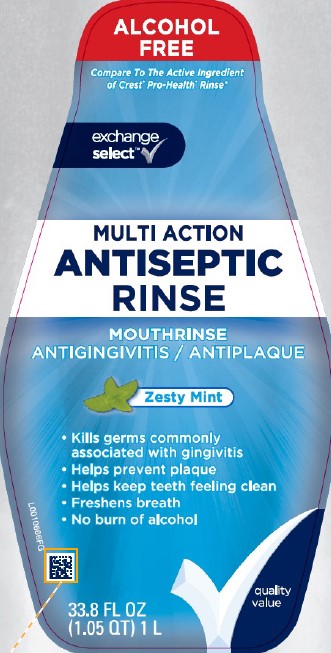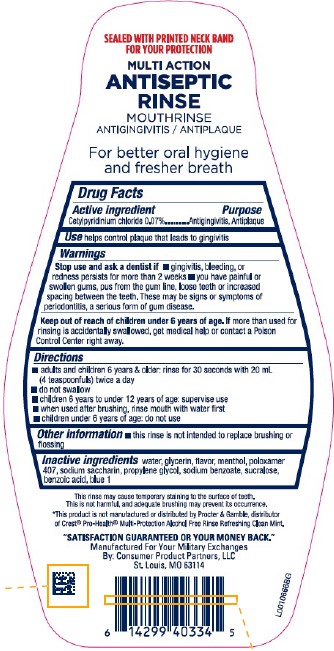 DRUG LABEL: Antiseptic
NDC: 55301-299 | Form: RINSE
Manufacturer: Your Military Exchanges
Category: otc | Type: HUMAN OTC DRUG LABEL
Date: 20260212

ACTIVE INGREDIENTS: CETYLPYRIDINIUM CHLORIDE 0.7 mg/1 mL
INACTIVE INGREDIENTS: WATER; GLYCERIN; MENTHOL, UNSPECIFIED FORM; POLOXAMER 407; SACCHARIN SODIUM; PROPYLENE GLYCOL; SODIUM BENZOATE; SUCRALOSE; BENZOIC ACID; FD&C BLUE NO. 1

Exchange Select 299.006/299AM
Multi Action Alcohol Free Antiseptic Rinse w/CPC

Tamper Evident Statement

SEALED WITH PRINTED NECK BAND FOR YOUR PROTECTION

Claims

MULTI ACTION ANTISEPTIC RINSE

MOUTHRINSE

ANTIGINGIVITIS/ANTIPLAQUE

For better oral hygiene and fresher breath

Active ingredient

Cetylpyridinium Chloride 0.07%

Purpose

Antigingivitis, Antiplaque

Use

helps control plaque that leads to gingivitis

Warnings

for this product

Stop use and ask a dentist if

- gingivitis, bleeding, or redness persists for more than 2 weeks
- you have painful or swollen gums, puss from the gum line, loose teeth or increaded spacing between the teeth. These may be signs or symptoms of periodontitis, a serious form of gum disease.

Keep out of reach of children under 6 years of age.

If more than used for rinsing is accidentally swallowed, get medical help or contact a Poison Control Center right away.

Directions

- adults and children 6 years & older: rinse for 30 seconds with 20 mL (4 teaspoonfuls) twice a day
- do not swallow
- children 6 years to under 12 years of age: supervise use
- when used after brushing, rinse mouth with water first
- children under 6 years of age: do not use

Other information

- this rinse is not intended to replace brushing or flossing

Inactive ingredients

water, glycerin, flavor, menthol, poloxamer 407, sodium saccharin, propylene glycol, sodium benzoate, sucralose, benzoic acid, blue 1

Disclaimers

This rinse may cause temporary staining to the surface of teeth.

This is not harmful, and adequate brushing may prevent its occurence.

*This product is not manufactured or distributed by Procter & Gamble, distributor of Crest®Pro-Health®Multi-Protection Alcohol Free Rinse Refreshing Clean Mint.

ADVERSE REACTION

"SATISFACTION GUARANTEED OR YOUR MONEY BACK."

Manufactured For Your Military Exchanges

By: Consumer Product Partners, LLC

St. Louis, MO 63114

principal display panel

ALCOHOL FREE

Compare To The Active Ingredient of Crest®Pro-Health®Rinse*

exchange select™

MULTI ACTION ANTISEPTIC RINSE

MOUTHRINSE

ANTIGINGIVITIS/ANTIPLAQUE

Zesty Mint

- Kills germs commonly associated with gingivitis
- Helps prevent plaque
- Helps keep teeth feeling clean
- Freshens breath
- No burn of alcohol

33.8 FL OZ (1.05 QT) 1 L

Quality Value